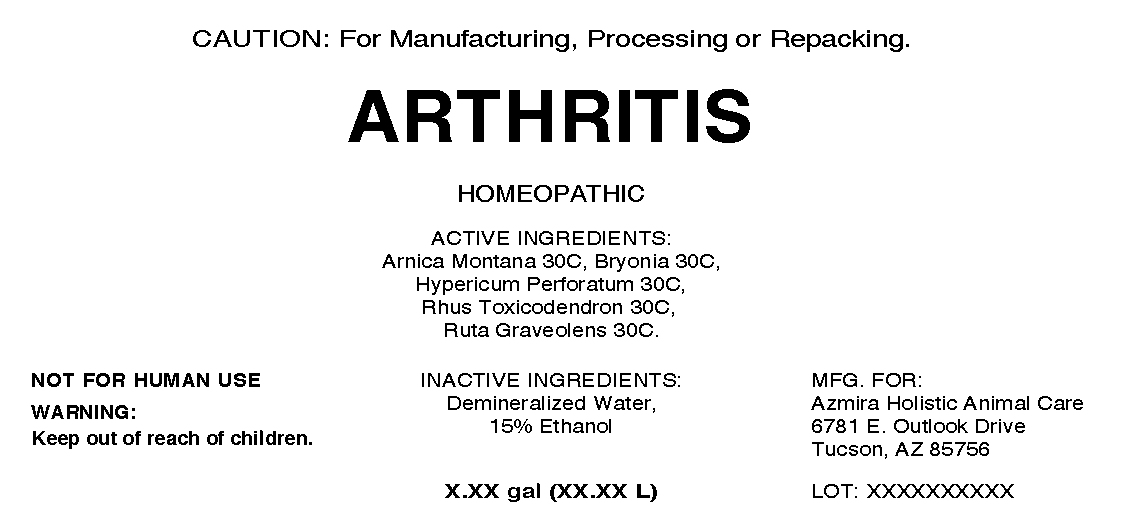 DRUG LABEL: Arthritis
NDC: 57520-0279 | Form: LIQUID
Manufacturer: Apotheca Company
Category: homeopathic | Type: OTC ANIMAL DRUG LABEL
Date: 20100625

ACTIVE INGREDIENTS: ARNICA MONTANA 30 [hp_C]/1 mL; BRYONIA ALBA ROOT 30 [hp_C]/1 mL; HYPERICUM PERFORATUM 30 [hp_C]/1 mL; TOXICODENDRON PUBESCENS LEAF 30 [hp_C]/1 mL; RUTA GRAVEOLENS FLOWERING TOP 30 [hp_C]/1 mL
INACTIVE INGREDIENTS: WATER; ALCOHOL

Arthritis

ACTIVE INGREDIENT

ACTIVE INGREDIENTS: Arnica Montana 30C, Bryonia 30C, Hypericum Perforatum 30C, Rhus Toxicodendron 30C, Ruta Graveolens 30C.

INACTIVE INGREDIENTS: Demineralized Water 15% Ethanol

QUESTIONS

MFG FOR:

Azmira Holistic Animal Care

6781 E. Outlook Drive

Tucson, AZ 85756

PACKAGE LABEL

CAUTION: For Manufacturing, Processing or Repacking

ARTHRITIS

HOMEOPATHIC

3830 ML

WARNINGS

NOT FOR HUMAN USE

WARNING:

Keep out of reach of children.